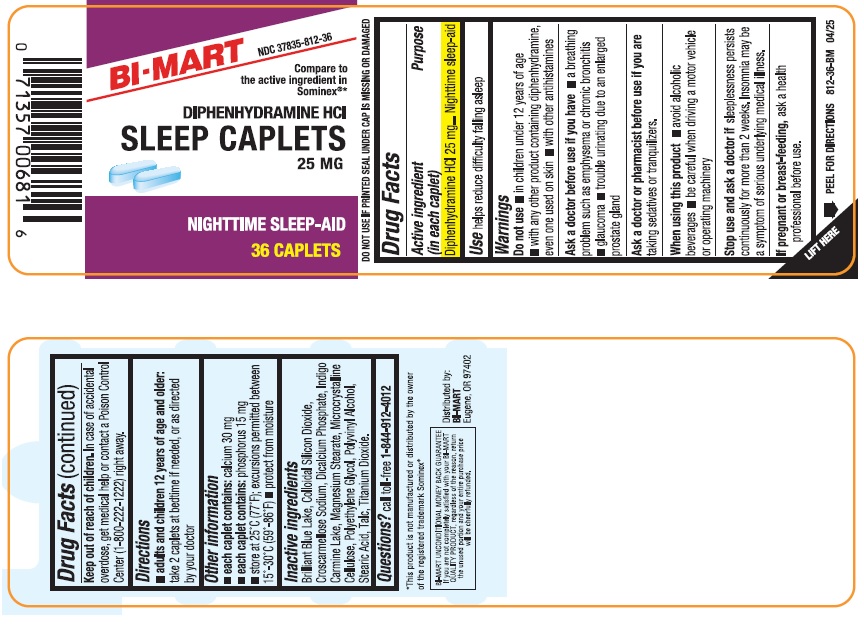 DRUG LABEL: NIGHTTIME SLEEP AID
NDC: 37835-812 | Form: TABLET
Manufacturer: Bi-Mart
Category: otc | Type: HUMAN OTC DRUG LABEL
Date: 20250501

ACTIVE INGREDIENTS: DIPHENHYDRAMINE HYDROCHLORIDE 25 mg/1 1
INACTIVE INGREDIENTS: SILICON DIOXIDE; CROSCARMELLOSE SODIUM; ANHYDROUS DIBASIC CALCIUM PHOSPHATE; MAGNESIUM STEARATE; CELLULOSE, MICROCRYSTALLINE; TITANIUM DIOXIDE; POLYVINYL ALCOHOL; POLYETHYLENE GLYCOL, UNSPECIFIED; TALC; STEARIC ACID; FD&C BLUE NO. 1; FD&C BLUE NO. 2

Active ingredient (in each caplet)

Diphenhydramine HCl 25 mg

Purpose

Nighttime sleep-aid

Use

help reduce difficult falling asleep

Warnings

Do not use

- in children under 12 years of age
- with any other products containing diphenhydramine, even one used on skin
- with other antihistamines

Ask a doctor before use if you have

- a breathing problem such as emphysema or chronic bronchitis
- glaucoma
- trouble urinating due to an enlarged prostate gland

Ask a doctor or pharmacist before use if you are

taking sedatives or tranquilizers.

When using this product

- avoid alcoholic beverages
- be careful when driveing a motor vehicle or operating machinery

Stop use and ask a doctor if

sleeplessness persists continuously for more than 2 weeks. Insomnia may be a symptom of a serious underlying medical illness.

If pregnant or breast-feeding,

ask a health professional before use.

Keep out of reach of children.

In case of accidental overdose, get medical help or contact a Poison Control Center (1-800-222-1222) right away.

Directions

- adults and children 12 years of age and older: take 2 caplets at bedtime if needed or as directed by a doctor

Other Information

- each caplet contains:calcium 30 mg
- each caplet contains:phosphorus 15 mg
- store at 25°C (77°F); excursions permitted between 15°-30°C (59°-86°F)
- protect from moisture

Inactive Ingredients

Briliant Blue Lack, Colloidal Silicon Dioxide, Croscarmellose Sodium, Dicalcium Phosphate, Indigo Carmine Lake, Magnesium Stearate, Microcrystalline Cellulose, Polyethylene Glycol, Polyvinyl Alcohol, Stearic Acid, Talc, Titanium Dioxide

Questions?

Call toll-free 1-844-912-4012

Distributed by:

BI-MART

Eugene, OR 97402